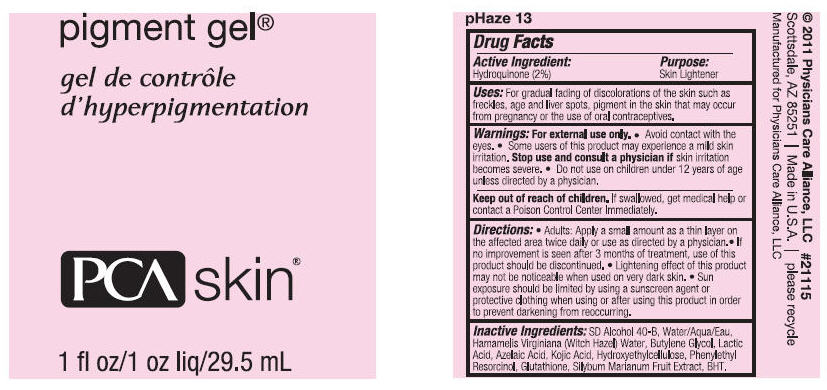 DRUG LABEL: PIGMENT
NDC: 65113-9003 | Form: GEL
Manufacturer: G.S. COSMECEUTICAL USA, INC.
Category: otc | Type: HUMAN OTC DRUG LABEL
Date: 20111115

ACTIVE INGREDIENTS: HYDROQUINONE 2 g/100 mL
INACTIVE INGREDIENTS: ALCOHOL; WATER; HAMAMELIS VIRGINIANA LEAF WATER; BUTYLENE GLYCOL; LACTIC ACID; AZELAIC ACID; KOJIC ACID; HYDROXYETHYL CELLULOSE (2000 MPA.S FOR 1% AQUEOUS SOLUTION); PHENYLETHYL RESORCINOL; GLUTATHIONE; SILYBUM MARIANUM SEED; BUTYLATED HYDROXYTOLUENE

pigment gel®

PRINCIPAL DISPLAY PANEL - 29.5 mL Label

pigment gel®

PCA skin®

1 fl oz/1 oz liq/29.5 mL